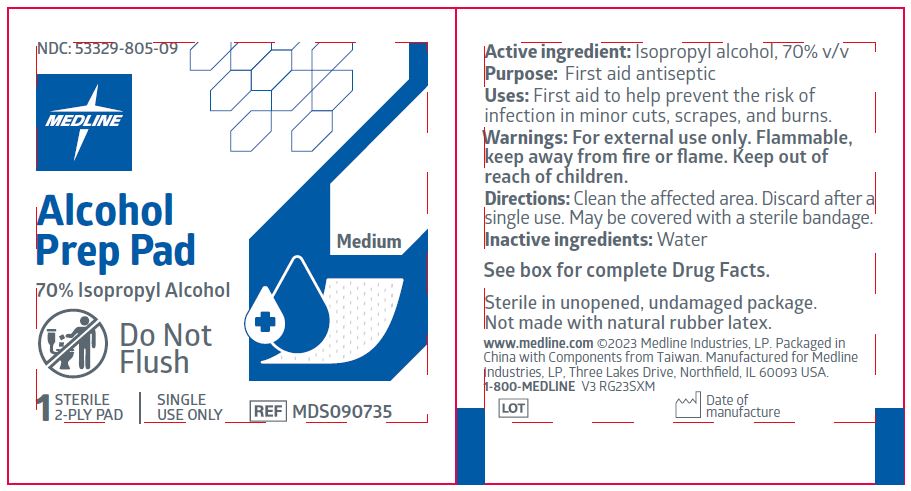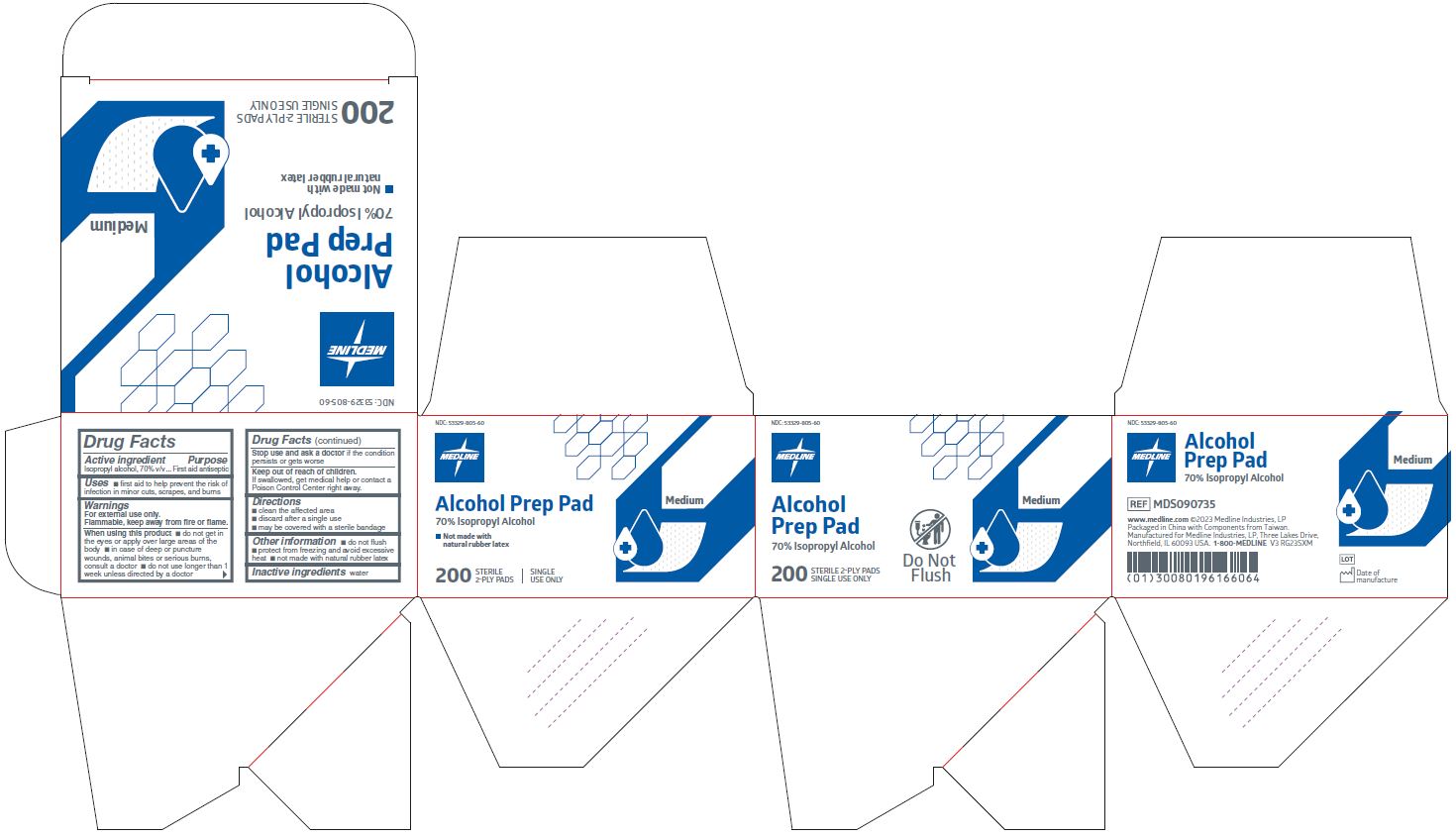 DRUG LABEL: Medline Alcohol Prep
NDC: 53329-805 | Form: SWAB
Manufacturer: Medline Industries, LP
Category: otc | Type: HUMAN OTC DRUG LABEL
Date: 20251016

ACTIVE INGREDIENTS: ISOPROPYL ALCOHOL 70 mL/100 mL
INACTIVE INGREDIENTS: WATER

805 Medline Sterile Isopropyl Prep Pads

Active ingredient

Isopropyl alcohol 70% v/v

Purpose

First aid antiseptic

Uses

- first aid antiseptic to help prevent infection in minor cuts, scrapes, and burns

Warnings

For external use only.

Flammable, keep away from fire or flame.

When using this product

- do not get in the eyes or apply over large areas of the body
- in case of deep or puncture wounds, animal bites or serious burns, consult a doctor
- do not use longer than 1 week unless directed by a doctor

Stop use and ask a doctor if

- the condition persists or gets worse

Keep out of reach of children.

If swallowed, get medical help or contact a Poison Control Center right away.

Directions

- clean the affected area
- discard after a single use
- may be covered with a sterile bandage

Other information

- do not flush
- protect from freezing and avoid excessive heat
- not made with natural rubber latex

Inactive ingredients

water

Manufacturing Information

www.medline.com

©2023 Medline Industries, LP

Made in China with Components from Taiwan

Manufactured for Medline Industries, LP

Three Lakes Drive, Northfield, IL 60093 USA

1-800-MEDLINE

REF: MDS090735